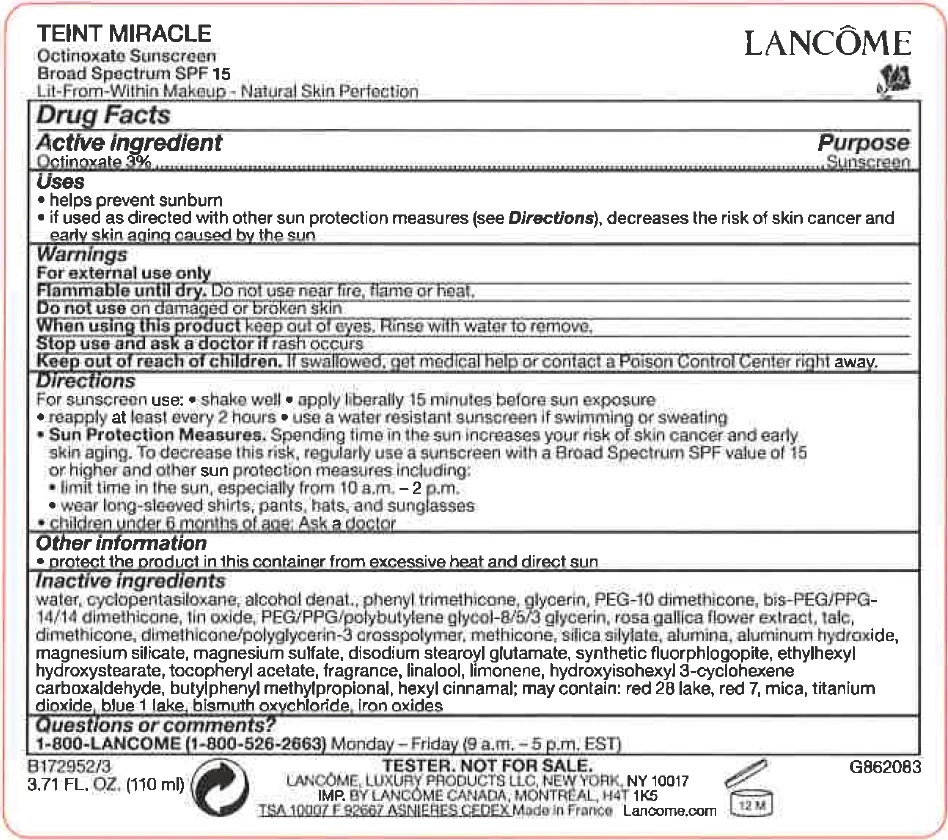 DRUG LABEL: Teint Miracle Octinoxate Sunscreen Broad Spectrum SPF 15
NDC: 70581-004 | Form: CREAM
Manufacturer: BPS 60
Category: otc | Type: HUMAN OTC DRUG LABEL
Date: 20231209

ACTIVE INGREDIENTS: OCTINOXATE 30 mg/1 mL
INACTIVE INGREDIENTS: MAGNESIUM SULFATE, UNSPECIFIED; DISODIUM STEAROYL GLUTAMATE; ETHYLHEXYL HYDROXYSTEARATE; .ALPHA.-TOCOPHEROL ACETATE; LINALOOL, (+/-)-; HYDROXYISOHEXYL 3-CYCLOHEXENE CARBOXALDEHYDE; BUTYLPHENYL METHYLPROPIONAL; .ALPHA.-HEXYLCINNAMALDEHYDE; WATER; CYCLOMETHICONE 5; ALCOHOL; PHENYL TRIMETHICONE; GLYCERIN; PEG-10 DIMETHICONE (600 CST); BIS-PEG/PPG-14/14 DIMETHICONE; STANNIC OXIDE; ROSA GALLICA FLOWER; TALC; DIMETHICONE; METHICONE (20 CST); ALUMINUM OXIDE; ALUMINUM HYDROXIDE; MAGNESIUM SILICATE

Teint Miracle Octinoxate Sunscreen Broad Spectrum SPF 15

Active ingredient

Octinoxate 3%

Purpose

Sunscreen

uses

- helps prevent sunburn
- if used as directed with other sun protection measures (see Directions), decreases the risk of skin cancer and early skin aging caused by the sun

Warnings

For external use only

Do not use near fire, flame or heat. Flammable untill dry.

DO not use

on damaged or broken skin

When using this product

keep out of eyes, Rinse with water to remove.

stop use and ask a doctor if

rash occurs.

Keep out of reach of children.

If swallowed, get medical help or contact a Poison Control Center right away.

Directions

For sunscreen use: •shake well • apply liberally 15 minutes before sun exposure • reaply at least every 2 hours • use a water resistant sunscreen if swimming or sweating • Spending time in the sun increases your risk of skin cancer and early skin aging. To decrease this risk. regularly use a sunscreen with a Broad Spectrum SPF value of 15 or higher and other sun protection measures including: • limit time in the sun. especially from 10 a.m. - 2 p.m. • wear long-sleeved shirts, pants, hats and sunglasses • children under 6 months of age: Ask a doctor
Sun Protection Measures.

Other information

- protect the product in this container from excessive heat and direct sun

Inactive ingredients

water, cyclopentasiloxane, alcohol denat., phenyl trimethicone, glycerin, PEG-10 dimethicone, bis-PEG/PPG-14/14 dimethicone, tin oxide, PEG/PPG/polybutylene glycol-8/5/3 glycerin, rosa gallica flower extract, talc, dimethicone, dimethicone/polyglycerin-3 crosspolymer, methicone, silica silylate, alumina, aluminum hydroxide, magnesium silicate, magnesium sulfate, disodium stearoyl glutamate, synthetic fluorphlogopite, ethylhexyl hydroxystearate, tocopheryl acetate, fragrance, linalool, limonene, hydroxyisohexyl 3-cyclohexene carboxaldehyde, butylphenyl methylpropional, hexyl cinnamal; may contain: red28 lake, red 7, mica, titanium dioxide, blue 1 lake, bismuth oxychloride, Iron oxides

Questions or comments?

1-800-LANCOME (1-800-526-2663) Monday - Friday (9 a.m. - 5 p.m. EST)